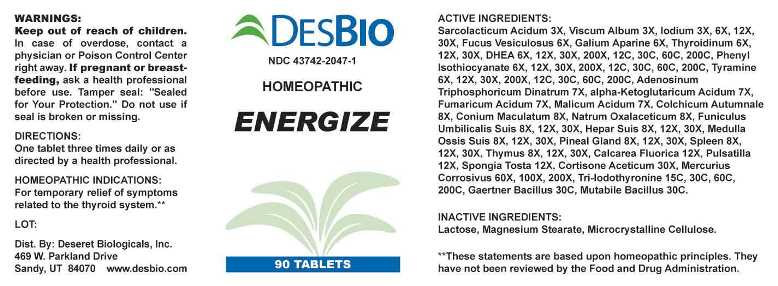 DRUG LABEL: Energize
NDC: 43742-2047 | Form: TABLET
Manufacturer: Deseret Biologicals
Category: homeopathic | Type: HUMAN OTC DRUG LABEL
Date: 20240117

ACTIVE INGREDIENTS: LACTIC ACID, L- 3 [hp_X]/1 1; VISCUM ALBUM FRUITING TOP 3 [hp_X]/1 1; IODINE 3 [hp_X]/1 1; FUCUS VESICULOSUS 6 [hp_X]/1 1; GALIUM APARINE WHOLE 6 [hp_X]/1 1; THYROID 6 [hp_X]/1 1; PRASTERONE 6 [hp_X]/1 1; PHENYL ISOTHIOCYANATE 6 [hp_X]/1 1; TYRAMINE 6 [hp_X]/1 1; ADENOSINE TRIPHOSPHATE DISODIUM 7 [hp_X]/1 1; OXOGLURIC ACID 7 [hp_X]/1 1; FUMARIC ACID 7 [hp_X]/1 1; MALIC ACID 7 [hp_X]/1 1; COLCHICUM AUTUMNALE BULB 8 [hp_X]/1 1; CONIUM MACULATUM FLOWERING TOP 8 [hp_X]/1 1; SODIUM DIETHYL OXALACETATE 8 [hp_X]/1 1; SUS SCROFA UMBILICAL CORD 8 [hp_X]/1 1; PORK LIVER 8 [hp_X]/1 1; SUS SCROFA BONE MARROW 8 [hp_X]/1 1; SUS SCROFA PINEAL GLAND 8 [hp_X]/1 1; SUS SCROFA SPLEEN 8 [hp_X]/1 1; SUS SCROFA THYMUS 8 [hp_X]/1 1; CALCIUM FLUORIDE 12 [hp_X]/1 1; PULSATILLA VULGARIS WHOLE 12 [hp_X]/1 1; SPONGIA OFFICINALIS SKELETON, ROASTED 12 [hp_X]/1 1; CORTISONE ACETATE 30 [hp_X]/1 1; MERCURIC CHLORIDE 60 [hp_X]/1 1; LIOTHYRONINE 15 [hp_C]/1 1; SALMONELLA ENTERICA SUBSP. ENTERICA SEROVAR ENTERITIDIS 30 [hp_C]/1 1; ESCHERICHIA COLI 30 [hp_C]/1 1
INACTIVE INGREDIENTS: LACTOSE MONOHYDRATE; MAGNESIUM STEARATE; CELLULOSE, MICROCRYSTALLINE

DRUG FACTS:

ACTIVE INGREDIENTS:

Sarcolacticum Acidum 3X, Viscum Album 3X, Iodium 3X, 6X, 12X, 30X, Fucus Vesiculosus 6X, Galium Aparine 6X, Thyroidinum (Suis) 6X, 12X, 30X, DHEA (Dehydroepiandrosterone) 6X, 12X, 30X, 200X, 12C, 30C, 60C, 200C, Phenyl Isothiocyanate 6X, 12X, 30X, 200X, 12C, 30C, 60C, 200C, Tyramine 6X, 12X, 30X, 200X, 12C, 30C, 60C, 200C, Adenosinum Triphosphoricum Dinatrum 7X, Alpha-Ketoglutaricum Acidum 7X, Fumaricum Acidum 7X, Malic Acidum 7X, Colchicum Autumnale 8X, Conium Maculatum 8X, Natrum Oxalaceticum 8X, Funiculus Umbilicalis Suis 8X, 12X, 30X, Hepar Suis 8X, 12X, 30X, Medulla Ossis Suis 8X, 12X, 30X, Pineal Gland (Suis) 8X, 12X, 30X, Spleen (Suis) 8X, 12X, 30X, Thymus (Suis) 8X, 12X, 30X, Calcarea Fluorica 12X, Pulsatilla (Vulgaris) 12X, Spongia Tosta 12X, Cortisone Aceticum 30X, Mercurius Corrosivus 60X, 100X, 200X, Tri-Iodothyronine 6X, 12X, 30X, 200X, 15C, 30C, 60C, 200C, Gaertner Bacillus (Bach) 30C, Mutabile Bacillus (Bach) 30C.

HOMEOPATHIC INDICATIONS:

For temporary relief of symptoms related to the thyroid system.**

**These statements are based upon homeopathic principles. They have not been reviewed by the Food and Drug Administration.

WARNINGS:

Keep out of reach of children. In case of overdose, contact a physician or Poison Control Center right away.

If pregnant or breast-feeding, ask a health professional before use.

Tamper seal: "Sealed for Your Protection." Do not use if seal is broken or missing.

Keep out of reach of children. In case of overdose, contact a physician or Poison Control Center right away.

DIRECTIONS:

One tablet three times daily or as directed by a health professional.

HOMEOPATHIC INDICATIONS:

For temporary relief of symptoms related to the thyroid system.**

**These statements are based upon homeopathic principles. They have not been reviewed by the Food and Drug Administration.

INACTIVE INGREDIENTS:

Lactose, Magnesium Stearate, Microcrystalline Cellulose.

QUESTIONS:

Dist. by Deseret Biologicals, Inc.

469 W. Parkland Drive

Sandy, UT 84070 www.desbio.com

PACKAGE LABEL DISPLAY:

DESBIO

NDC 43742-2047-1

HOMEOPATHIC

ENERGIZE

90 TABLETS